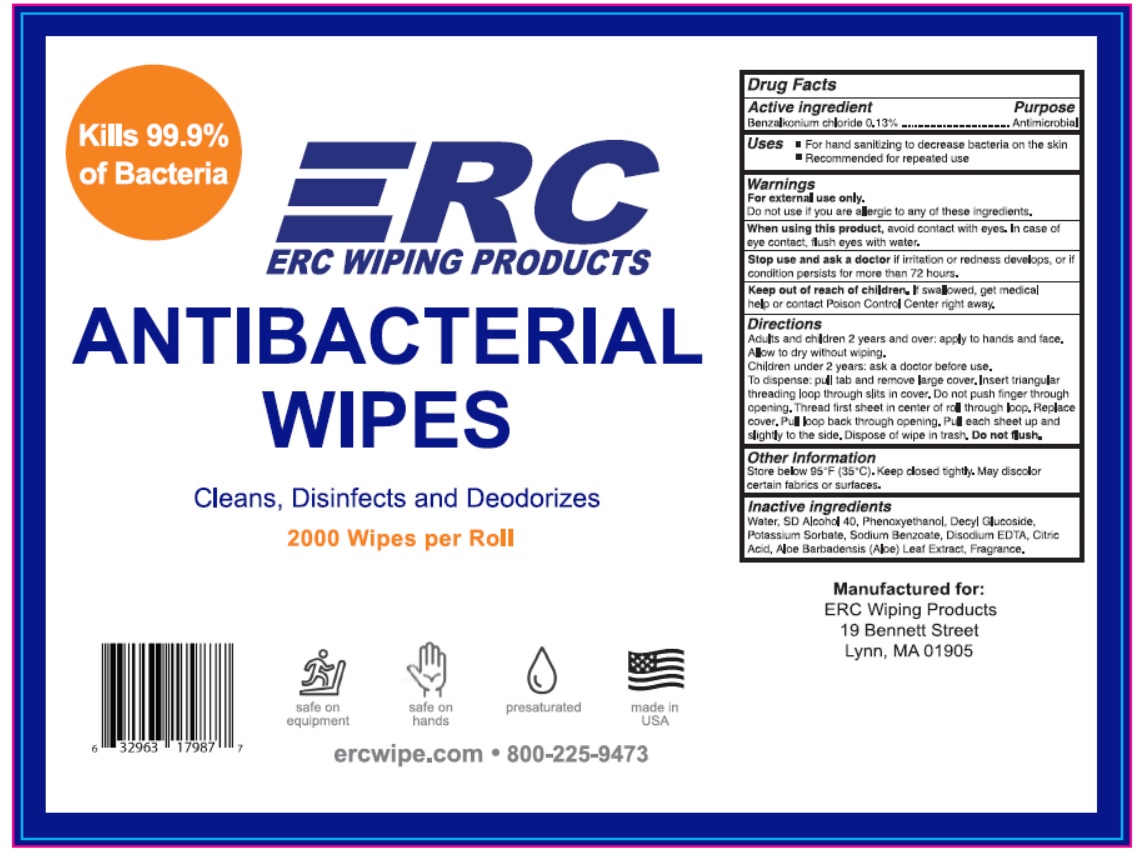 DRUG LABEL: Antibacterial Wipes
NDC: 71293-020 | Form: SWAB
Manufacturer: ERC Acquisition, Inc
Category: otc | Type: HUMAN OTC DRUG LABEL
Date: 20251205

ACTIVE INGREDIENTS: BENZALKONIUM CHLORIDE 0.13 g/100 g
INACTIVE INGREDIENTS: WATER; PHENOXYETHANOL; DECYL GLUCOSIDE; POTASSIUM SORBATE; SODIUM BENZOATE; EDETATE DISODIUM; CITRIC ACID MONOHYDRATE; ALOE VERA LEAF

Drug Facts

Active ingredient

Benzalkonium chloride 0.13%

Purpose

Antimicrobial

Uses

- For hand sanitizing to decrease bacteria on the skin
- Recommended for repeated use

Warnings

For external use only

Do not use if

you are allergic to any of this product

When using this product

avoid contact with eyes. In case of eye contact, flush eyes with water.

Stop use and ask a doctor

If irritation or redness develops, or if condition persists for more than 72 hours.

Keep out of reach of children

If swallowed, get medical help or contact a Poison Control Center immediately.

Directions

Adults and Children 2 years and over: apply to hands and face. Allow to dry without wiping.

Children under 2 years: ask a doctor before use

To dispense: pull tab and remove large cover. Insert triangular threading loop through slits in cover. Do not push finger through the opening. Thread first sheet in center or roll through loop. Replace cover. Pull loop back through opening. Pull each sheet up and slightly to the side. Dispose of wipe in trash. Do not flush.

Other information

Store below 95oF (35oC). keep closed tightly. May discolor certain fabric or surfaces

Inactive ingredients

Water, SD Alcohol 40, Phenoxyethanol, Decyl Glucoside, Potassium Sorbate, Sodium Benzoate, Disodium EDTA, Citric Acid, Aloe Barbadensis (Aloe) Leaf Extract, Fragrance.

Principal Display Panel

NDC 71293-020-01

2000 count

ERC

ERC WIPING PRODUCTS

KILLS 99.9% OF GERMS

ANTIBACTERIAL WIPES

Cleans, Disinfects and Deodorizes

2000 Wipes per roll

- safe on equipment
- safe on hands
- presaturated
- made in USA

ercwipe.com 800-225-9473